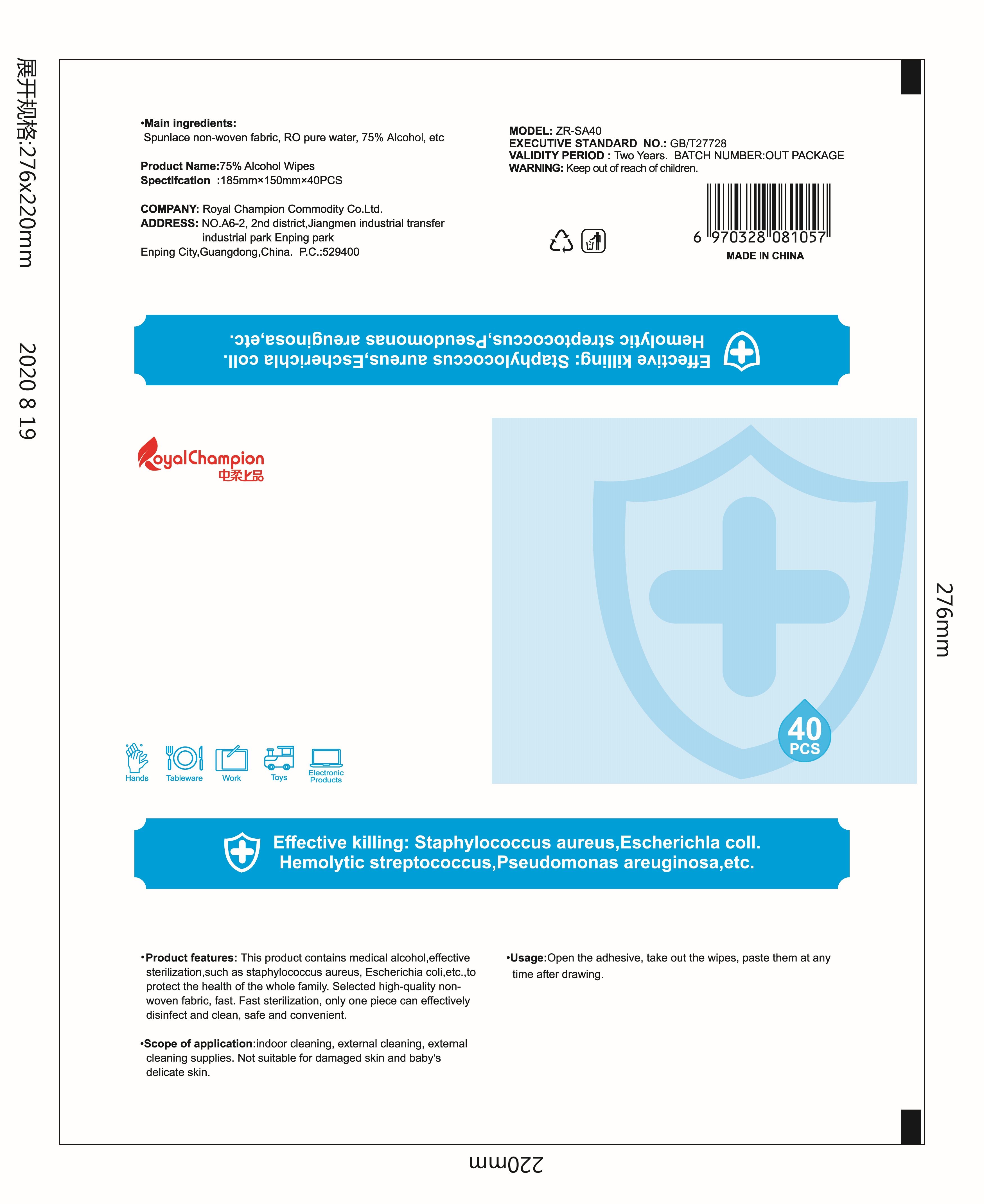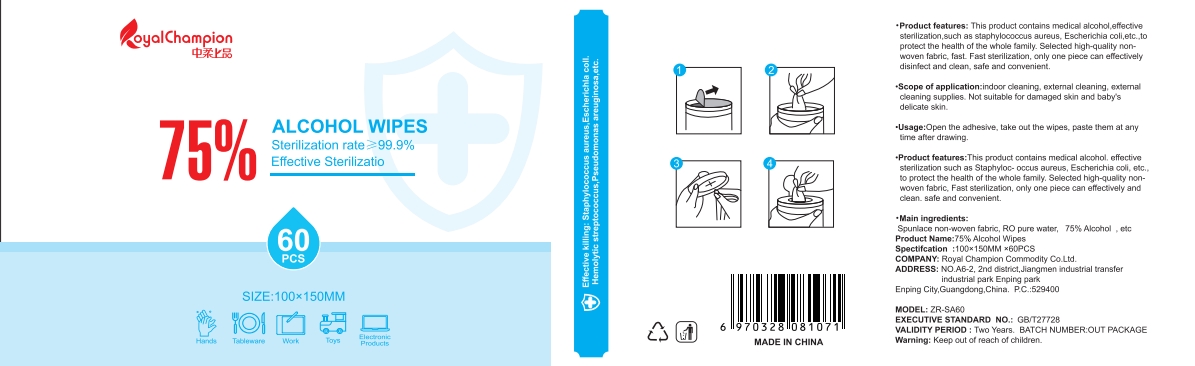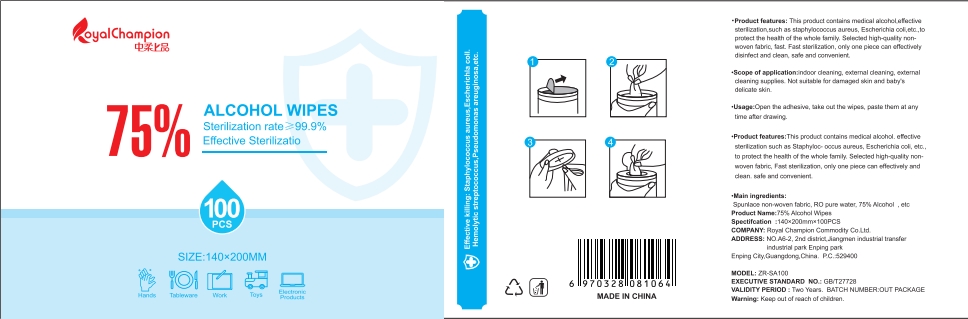 DRUG LABEL: 75% Alcohol Wipes
NDC: 41730-001 | Form: CLOTH
Manufacturer: Royal Champion Commodity Co.Ltd.
Category: otc | Type: HUMAN OTC DRUG LABEL
Date: 20201009

ACTIVE INGREDIENTS: ALCOHOL 200 mL/40 1
INACTIVE INGREDIENTS: WATER

DOSAGE AND ADMINISTRATION

Store in a cool and dry place.

INACTIVE INGREDIENT

Pure Water,Spunlace non-woven fabrice

INDICATIONS AND USAGE

Open the adhesive, take out the wipes, paste them at any time after drawing.

ACTIVE INGREDIENT

Ethyl Alcohol

keep out of reach of children

PURPOSE

Disinfection
Sterilization
No Rinseing

WARNINGS

Flammable,keep away from fire or flame. For external use only.